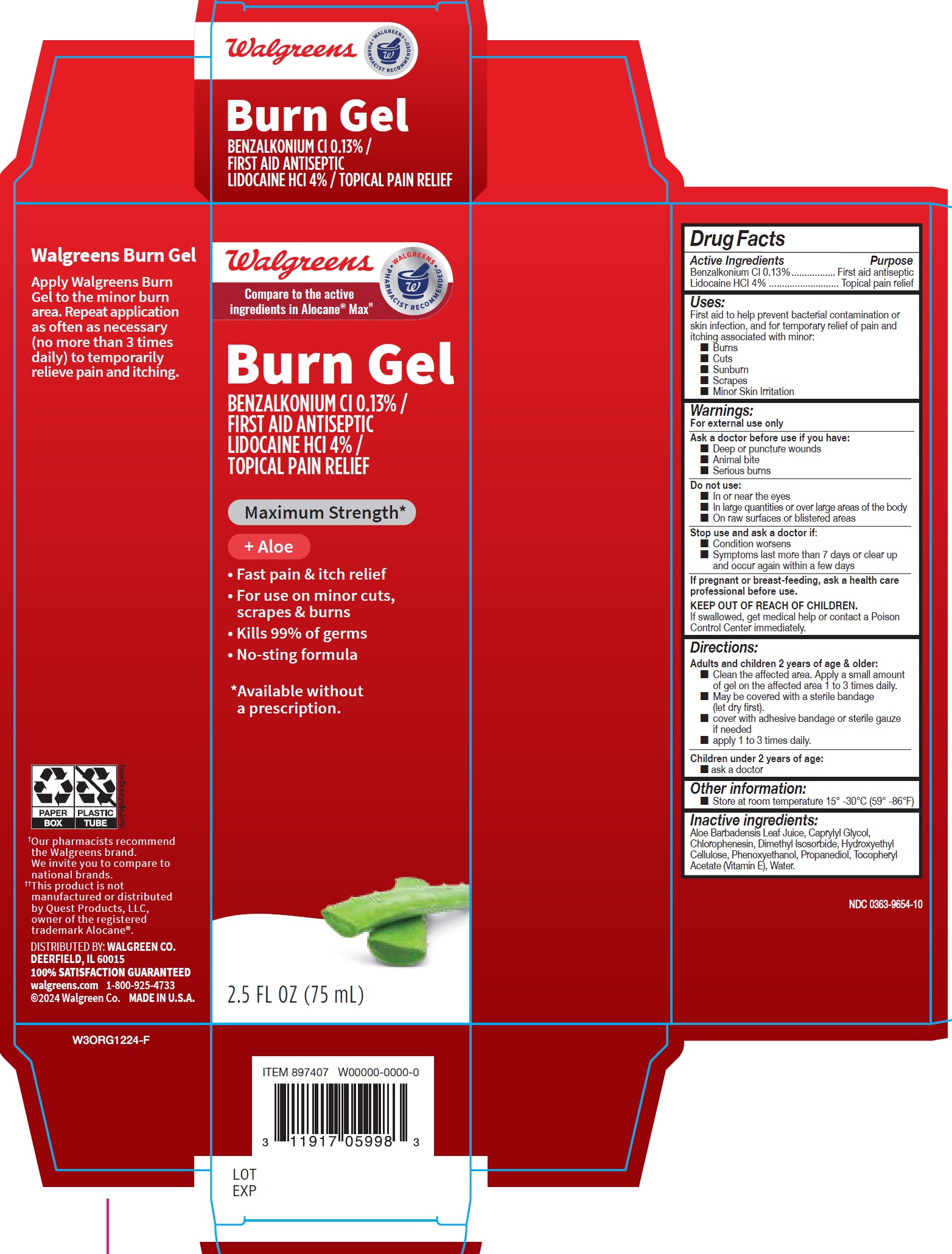 DRUG LABEL: Walgreens Max Strength Burn Gel
NDC: 0363-9654 | Form: GEL
Manufacturer: Walgreens Co.
Category: otc | Type: HUMAN OTC DRUG LABEL
Date: 20250407

ACTIVE INGREDIENTS: BENZALKONIUM CHLORIDE 13 mg/1 mL; LIDOCAINE HYDROCHLORIDE 40 mg/1 mL
INACTIVE INGREDIENTS: ALOE VERA LEAF JUICE; CAPRYLYL GLYCOL; CHLORPHENESIN; DIMETHYL ISOSORBIDE; HYDROXYETHYL CELLULOSE, UNSPECIFIED; PHENOXYETHANOL; PROPANEDIOL; .ALPHA.-TOCOPHEROL ACETATE; WATER

Walgreens Max Strength Burn Gel

Active Ingredients

Benzalkonium Cl 0.13%

Lidocaine HCI 4%

Purpose

First aid antiseptic

Topical pain relief

Uses:

First aid to help prevent bacterial contamination or skin infection, and for temporary relief of pain and itching associated with minor:

- Burns
- Cuts
- Sunburn
- Scrapes
- Minor Skin Irritation

Warnings

For external use only

Ask a doctor before use if you have:

- Deep or puncture wounds
- Animal bite
- Serious burns

Do not use:

- In or near the eyes
- In large quantities or over large areas of the body
- On raw surfaces or blistered areas

Stop use and ask a doctor if:

- Condition worsens
- Symptoms last more than 7 days or clear up and occur again within a few days

If pregnant or breast-feeding,

ask a health care professional before use.

KEEP OUT OF REACH OF CHILDREN.

If swallowed, get medical help or contact a Poison Control Center immediately.

Directions:

Adults and children 2 years of age & older:

- Clean the affected area. Apply a small amount of gel on the affected area 1 to 3 times daily.
- May be covered with a sterile bandage (let dry first).
- cover with adhesive bandage or sterile gauze if needed
- apply 1 to 3 times daily.

Children under 2 years of age:

- ask a doctor

Other information:

- Store at room temperature 15° -30°C (59° -86°F)

Inactive ingredients:

Aloe Barbadensis Leaf Juice, Caprylyl Glycol, Chlorophenesin, Dimethyl lsosorbide, Hydroxyethyl Cellulose, Phenoxyethanol, Propanediol, Tocopheryl Acetate (Vitamin E), Water.